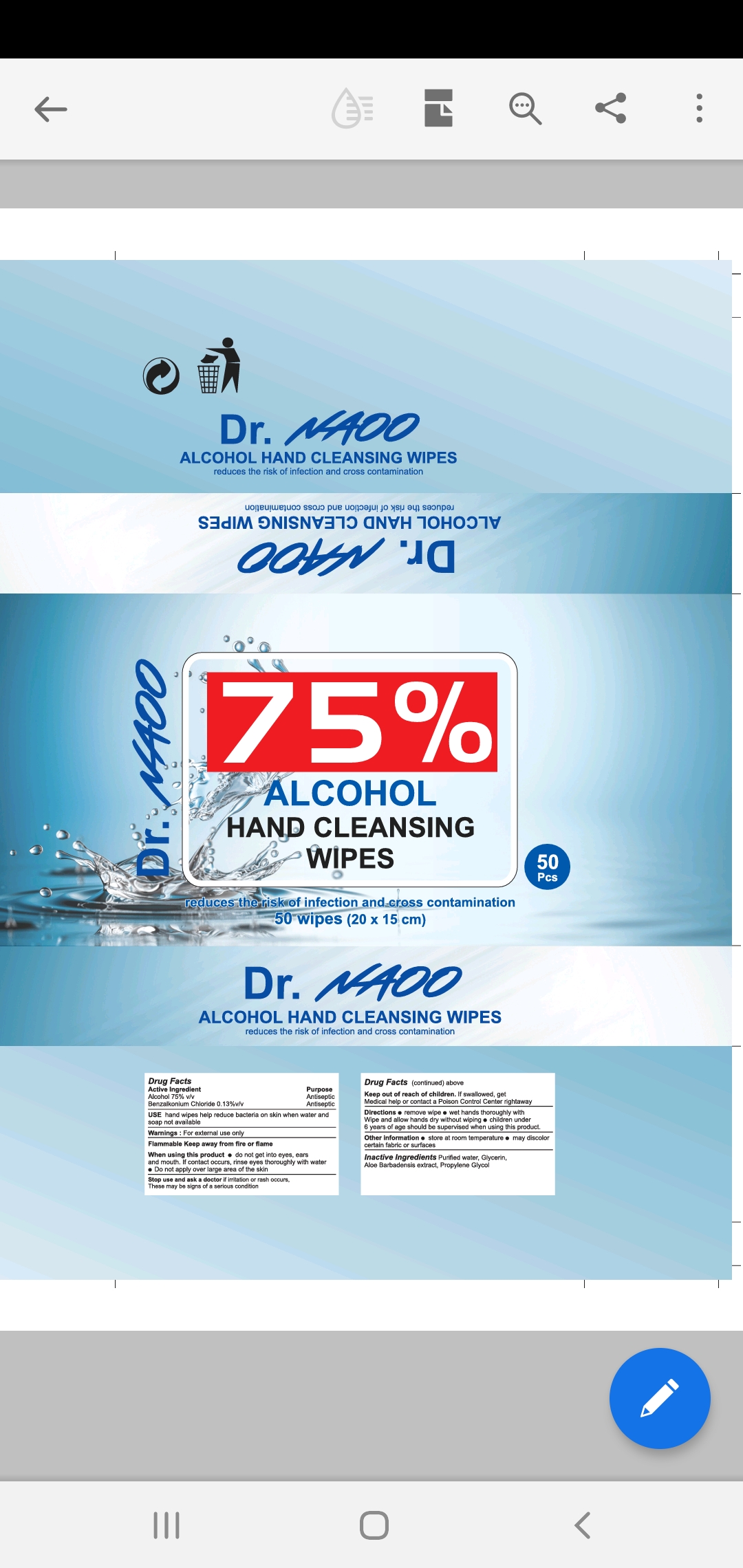 DRUG LABEL: Alcohol Hand Wipes
NDC: 79822-001 | Form: CLOTH
Manufacturer: NATION AMERICA OUTFITTERS LLC
Category: otc | Type: HUMAN OTC DRUG LABEL
Date: 20200724

ACTIVE INGREDIENTS: BENZALKONIUM CHLORIDE 0.05 g/100 g; ALCOHOL 75 g/100 g
INACTIVE INGREDIENTS: GLYCERIN; PROPYLENE GLYCOL ETHYL ETHER; WATER; ALOE

Active Ingredient(s)

Alcohol 75% v/v. Purpose: Antiseptic

BENZALKONIUM CHLORIDE 0.05% v/v. Purpose: Antiseptic

Purpose

Antiseptic, Alcohol Wipes

Use

Alcohol Wipes to help reduce bacteria that potentially can cause disease. For use when soap and water are not available.

Warnings

For external use only. Flammable. Keep away from heat or flame

Do not use

- in children less than 2 months of age
- on open skin wounds

When using this product keep out of eyes, ears, and mouth. In case of contact with eyes, rinse eyes thoroughly with water.
Stop use and ask a doctor if irritation or rash occurs. These may be signs of a serious condition.
Keep out of reach of children. If swallowed, get medical help or contact a Poison Control Center right away.

Stop use and ask a doctor if irritation or rash occurs. These may be signs of a serious condition.

Keep out of reach of children. If swallowed, get medical help or contact a Poison Control Center right away.

Directions

- Wipe product on hands to cover all surfaces. Rub hands together until dry.
- Supervise children under 6 years of age when using this product to avoid swallowing.

Other information

- Store between 15-30C (59-86F)
- Avoid freezing and excessive heat above 40C (104F)

Inactive ingredients

purified water USP,glycerin,Aloe,Propylene Glycol,

Package Label - Principal Display Panel

50 Wipes NDC: 79822-001-50